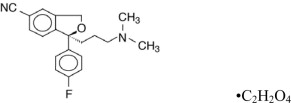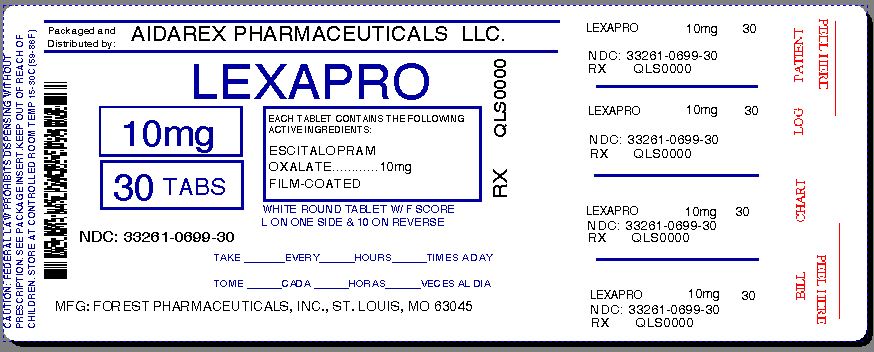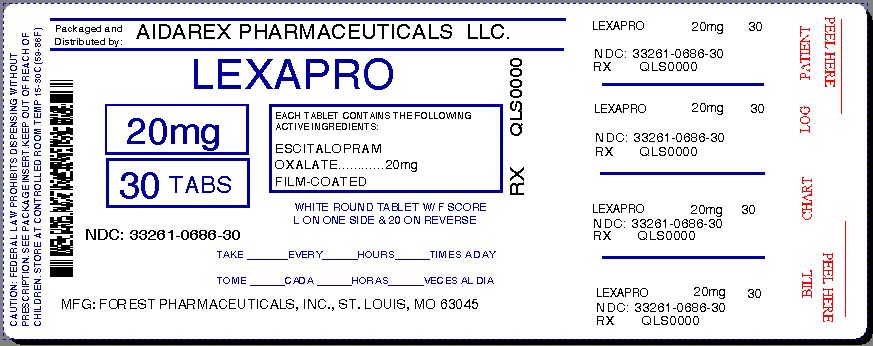 DRUG LABEL: Lexapro
NDC: 33261-699 | Form: TABLET, FILM COATED
Manufacturer: Aidarex Pharmaceuticals LLC
Category: prescription | Type: HUMAN PRESCRIPTION DRUG LABEL
Date: 20140108

ACTIVE INGREDIENTS: ESCITALOPRAM OXALATE 10 mg/1 1
INACTIVE INGREDIENTS: TALC; CROSCARMELLOSE SODIUM; CELLULOSE, MICROCRYSTALLINE; SILICON DIOXIDE; MAGNESIUM STEARATE; HYPROMELLOSES; TITANIUM DIOXIDE; POLYETHYLENE GLYCOLS

HIGHLIGHTS OF PRESCRIBING INFORMATION

These highlights do not include all the information needed to use Lexapro® safely and effectively. See full prescribing information for Lexapro®
Lexapro® (escitalopram oxalate) Tablets
Lexapro® (escitalopram oxalate) Oral Solution
Initial U.S. Approval: 2002

RECENT MAJOR CHANGES

- Dosage and Administration (2.5, 2.6) 12/2012
- Contraindications (4.1) 12/2012
- Warnings and Precautions (5.2) 12/2012

WARNINGS: SUICIDALITY AND ANTIDEPRESSANT DRUGS

WARNING: Suicidality and Antidepressant Drugs

See full prescribing information for complete boxed warning.

Increased risk of suicidal thinking and behavior in children, adolescents and young adults taking antidepressants for major depressive disorder (MDD) and other psychiatric disorders. Lexapro is not approved for use in pediatric patients less than 12 years of age (5.1).

1 INDICATIONS AND USAGE

Lexapro® is a selective serotonin reuptake inhibitor (SSRI) indicated for:

- Acute and Maintenance Treatment of Major Depressive Disorder (MDD) in adults and adolescents aged 12-17 years (1.1)
- Acute Treatment of Generalized Anxiety Disorder (GAD) in adults (1.2)

2 DOSAGE AND ADMINISTRATION

Lexapro should generally be administered once daily, morning or evening with or without food (2.1, 2.2).

Indication | Recommended Dose
MDD (2.1)
Adolescents (2.1) | Initial: 10 mg once daily; Recommended: 10 mg once daily; Maximum: 20 mg once daily
Adults (2.1) | Initial: 10 mg once daily; Recommended: 10 mg once daily; Maximum: 20 mg once daily
GAD (2.2)
Adults (2.2) | Initial: 10 mg once daily; Recommended: 10 mg once daily

- No additional benefits seen at 20 mg/day dose (2.1).
- 10 mg/day is the recommended dose for most elderly patients and patients with hepatic impairment (2.3).
- No dosage adjustment for patients with mild or moderate renal impairment. Use caution in patients with severe renal impairment (2.3).
- Discontinuing Lexapro: A gradual dose reduction is recommended (2.4).

3 DOSAGE FORMS AND STRENGTHS

- Tablets: 5 mg, 10 mg (scored) and 20 mg (scored) (3.1)
- Oral solution: 1 mg per mL (3.2)

4 CONTRAINDICATIONS

- Serotonin Syndrome and MAOIs: Do not use MAOIs intended to treat psychiatric disorders with Lexapro or within 14 days of stopping treatment with Lexapro. Do not use Lexapro within 14 days of stopping an MAOI intended to treat psychiatric disorders. In addition, do not start Lexapro in a patient who is being treated with linezolid or intravenous methylene blue (4.1).
- Pimozide: Do not use concomitantly (4.2).
- Known hypersensitivity to escitalopram or citalopram or any of the inactive ingredients (4.3).

5 WARNINGS AND PRECAUTIONS

- Clinical Worsening/Suicide Risk: Monitor for clinical worsening, suicidality and unusual change in behavior, especially, during the initial few months of therapy or at times of dose changes (5.1).
- Serotonin Syndrome: Serotonin syndrome has been reported with SSRIs and SNRIs, including Lexapro, both when taken alone, but especially when co-administered with other serotonergic agents (including triptans, tricyclic antidepressants, fentanyl, lithium, tramadol, tryptophan, buspirone and St. John's Wort). If such symptoms occur, discontinue Lexapro and initiate supportive treatment. If concomitant use of Lexapro with other serotonergic drugs is clinically warranted, patients should be made aware of a potential increased risk for serotonin syndrome, particularly during treatment initiation and dose increases (5.2).
- Discontinuation of Treatment with Lexapro: A gradual reduction in dose rather than abrupt cessation is recommended whenever possible (5.3).
- Seizures: Prescribe with care in patients with a history of seizure (5.4).
- Activation of Mania/Hypomania: Use cautiously in patients with a history of mania (5.5).
- Hyponatremia: Can occur in association with SIADH (5.6).
- Abnormal Bleeding: Use caution in concomitant use with NSAIDs, aspirin, warfarin or other drugs that affect coagulation (5.7).
- Interference with Cognitive and Motor Performance: Use caution when operating machinery (5.8).
- Use in Patients with Concomitant Illness: Use caution in patients with diseases or conditions that produce altered metabolism or hemodynamic responses (5.9).

6 ADVERSE REACTIONS

Most commonly observed adverse reactions (incidence ≥ 5% and at least twice the incidence of placebo patients) are: insomnia, ejaculation disorder (primarily ejaculatory delay), nausea, sweating increased, fatigue and somnolence, decreased libido, and anorgasmia (6.1).

To report SUSPECTED ADVERSE REACTIONS, contact Forest Laboratories Inc. at 1-800-678-1605, or FDA at 1-800-FDA-1088 or www.fda.gov/medwatch .

7 DRUG INTERACTIONS

Concomitant use with SSRIs, SNRIs or Tryptophan is not recommended (7.2).

Use caution when concomitant use with drugs that affect Hemostasis (NSAIDs, Aspirin, Warfarin) (7.6).

8 USE IN SPECIFIC POPULATIONS

Pregnancy: Use only if the potential benefit justifies the potential risk to the fetus (8.1).

Nursing Mothers: Caution should be exercised when administered to a nursing woman (8.3)

Pediatric Use: Safety and effectiveness of Lexapro has not been established in pediatric MDD patients less than 12 years of age (8.4).

FULL PRESCRIBING INFORMATION

WARNINGS: SUICIDALITY AND ANTIDEPRESSANT DRUGS

Antidepressants increased the risk compared to placebo of suicidal thinking and behavior (suicidality) in children, adolescents, and young adults in short-term studies of major depressive disorder (MDD) and other psychiatric disorders. Anyone considering the use of Lexapro or any other antidepressant in a child, adolescent, or young adult must balance this risk with the clinical need. Short-term studies did not show an increase in the risk of suicidality with antidepressants compared to placebo in adults beyond age 24; there was a reduction in risk with antidepressants compared to placebo in adults aged 65 and older. Depression and certain other psychiatric disorders are themselves associated with increases in the risk of suicide. Patients of all ages who are started on antidepressant therapy should be monitored appropriately and observed closely for clinical worsening, suicidality, or unusual changes in behavior. Families and caregivers should be advised of the need for close observation and communication with the prescriber. Lexapro is not approved for use in pediatric patients less than 12 years of age.[See Warnings and Precautions: Clinical Worsening and Suicide Risk (5.1), Patient Counseling Information: Information for Patients (17.1), and Use in Specific Populations: Pediatric Use (8.4)].

1 INDICATIONS AND USAGE

1.1 Major Depressive Disorder

Lexapro (escitalopram) is indicated for the acute and maintenance treatment of major depressive disorder in adults and in adolescents 12 to 17 years of age [see Clinical Studies (14.1)].

A major depressive episode (DSM-IV) implies a prominent and relatively persistent (nearly every day for at least 2 weeks) depressed or dysphoric mood that usually interferes with daily functioning, and includes at least five of the following nine symptoms: depressed mood, loss of interest in usual activities, significant change in weight and/or appetite, insomnia or hypersomnia, psychomotor agitation or retardation, increased fatigue, feelings of guilt or worthlessness, slowed thinking or impaired concentration, a suicide attempt or suicidal ideation.

1.2 Generalized Anxiety Disorder

Lexapro is indicated for the acute treatment of Generalized Anxiety Disorder (GAD) in adults [see Clinical Studies (14.2)].

Generalized Anxiety Disorder (DSM-IV) is characterized by excessive anxiety and worry (apprehensive expectation) that is persistent for at least 6 months and which the person finds difficult to control. It must be associated with at least 3 of the following symptoms: restlessness or feeling keyed up or on edge, being easily fatigued, difficulty concentrating or mind going blank, irritability, muscle tension, and sleep disturbance.

2 DOSAGE AND ADMINISTRATION

Lexapro should be administered once daily, in the morning or evening, with or without food.

2.1 Major Depressive Disorder

Initial Treatment

Adolescents

The recommended dose of Lexapro is 10 mg once daily. A flexible-dose trial of Lexapro (10 to 20 mg/day) demonstrated the effectiveness of Lexapro [see Clinical Studies (14.1)]. If the dose is increased to 20 mg, this should occur after a minimum of three weeks.

Adults

The recommended dose of Lexapro is 10 mg once daily. A fixed-dose trial of Lexapro demonstrated the effectiveness of both 10 mg and 20 mg of Lexapro, but failed to demonstrate a greater benefit of 20 mg over 10 mg [see Clinical Studies (14.1)]. If the dose is increased to 20 mg, this should occur after a minimum of one week.

Maintenance Treatment

It is generally agreed that acute episodes of major depressive disorder require several months or longer of sustained pharmacological therapy beyond response to the acute episode. Systematic evaluation of continuing Lexapro 10 or 20 mg/day in adults patients with major depressive disorder who responded while taking Lexapro during an 8-week, acute-treatment phase demonstrated a benefit of such maintenance treatment [see Clinical Studies (14.1)]. Nevertheless, the physician who elects to use Lexapro for extended periods should periodically re-evaluate the long-term usefulness of the drug for the individual patient. Patients should be periodically reassessed to determine the need for maintenance treatment.

2.2 Generalized Anxiety Disorder

Initial Treatment

Adults

The recommended starting dose of Lexapro is 10 mg once daily. If the dose is increased to 20 mg, this should occur after a minimum of one week.

Maintenance Treatment

Generalized anxiety disorder is recognized as a chronic condition. The efficacy of Lexapro in the treatment of GAD beyond 8 weeks has not been systematically studied. The physician who elects to use Lexapro for extended periods should periodically re-evaluate the long-term usefulness of the drug for the individual patient.

2.3 Special Populations

10 mg/day is the recommended dose for most elderly patients and patients with hepatic impairment.

No dosage adjustment is necessary for patients with mild or moderate renal impairment. Lexapro should be used with caution in patients with severe renal impairment.

2.4 Discontinuation of Treatment with Lexapro

Symptoms associated with discontinuation of Lexapro and other SSRIs and SNRIs have been reported [see Warnings and Precautions (5.3)]. Patients should be monitored for these symptoms when discontinuing treatment. A gradual reduction in the dose rather than abrupt cessation is recommended whenever possible. If intolerable symptoms occur following a decrease in the dose or upon discontinuation of treatment, then resuming the previously prescribed dose may be considered. Subsequently, the physician may continue decreasing the dose but at a more gradual rate.

2.5 Switching a Patient To or From a Monoamine Oxidase Inhibitor (MAOI) Intended to Treat Psychiatric Disorders

At least 14 days should elapse between discontinuation of an MAOI intended to treat psychiatric disorders and initiation of therapy with Lexapro. Conversely, at least 14 days should be allowed after stopping Lexapro before starting an MAOI intended to treat psychiatric disorders [see Contraindications (4.1)].

2.6 Use of Lexapro with Other MAOIs such as Linezolid or Methylene Blue

Do not start Lexapro in a patient who is being treated with linezolid or intravenous methylene blue because there is an increased risk of serotonin syndrome. In a patient who requires more urgent treatment of a psychiatric condition, other interventions, including hospitalization, should be considered [see Contraindications (4.1)].

In some cases, a patient already receiving Lexapro therapy may require urgent treatment with linezolid or intravenous methylene blue. If acceptable alternatives to linezolid or intravenous methylene blue treatment are not available and the potential benefits of linezolid or intravenous methylene blue treatment are judged to outweigh the risks of serotonin syndrome in a particular patient, Lexapro should be stopped promptly, and linezolid or intravenous methylene blue can be administered. The patient should be monitored for symptoms of serotonin syndrome for 2 weeks or until 24 hours after the last dose of linezolid or intravenous methylene blue, whichever comes first. Therapy with Lexapro may be resumed 24 hours after the last dose of linezolid or intravenous methylene blue [see Warnings and Precautions (5.2)].

The risk of administering methylene blue by non-intravenous routes (such as oral tablets or by local injection) or in intravenous doses much lower than 1 mg/kg with Lexapro is unclear. The clinician should, nevertheless, be aware of the possibility of emergent symptoms of serotonin syndrome with such use [see Warnings and Precautions (5.2)].

3 DOSAGE FORMS AND STRENGTHS

3.1 Tablets

Lexapro tablets are film-coated, round tablets containing escitalopram oxalate in strengths equivalent to 5 mg, 10 mg and 20 mg escitalopram base. The 10 and 20 mg tablets are scored. Imprinted with "FL" on one side and either "5", “10”, or “20” on the other side according to their respective strengths.

3.2 Oral Solution

Lexapro oral solution contains escitalopram oxalate equivalent to 1 mg/mL escitalopram base.

4 CONTRAINDICATIONS

4.1 Monoamine Oxidase Inhibitors (MAOIs)

The use of MAOIs intended to treat psychiatric disorders with Lexapro or within 14 days of stopping treatment with Lexapro is contraindicated because of an increased risk of serotonin syndrome. The use of Lexapro within 14 days of stopping an MAOI intended to treat psychiatric disorders is also contraindicated [see Dosage and Administration (2.5), and Warnings and Precautions (5.2)].

Starting Lexapro in a patient who is being treated with MAOIs such as linezolid or intravenous methylene blue is also contraindicated because of an increased risk of serotonin syndrome [see Dosage and Administration (2.6), and Warnings and Precautions (5.2)].

4.2 Pimozide

Concomitant use in patients taking pimozide is contraindicated [see Drug Interactions (7.10)].

4.3 Hypersensitivity to escitalopram or citalopram

Lexapro is contraindicated in patients with a hypersensitivity to escitalopram or citalopram or any of the inactive ingredients in Lexapro.

5 WARNINGS AND PRECAUTIONS

5.1 Clinical Worsening and Suicide Risk

Patients with major depressive disorder (MDD), both adult and pediatric, may experience worsening of their depression and/or the emergence of suicidal ideation and behavior (suicidality) or unusual changes in behavior, whether or not they are taking antidepressant medications, and this risk may persist until significant remission occurs. Suicide is a known risk of depression and certain other psychiatric disorders, and these disorders themselves are the strongest predictors of suicide. There has been a long-standing concern, however, that antidepressants may have a role in inducing worsening of depression and the emergence of suicidality in certain patients during the early phases of treatment. Pooled analyses of short-term placebo-controlled trials of antidepressant drugs (SSRIs and others) showed that these drugs increase the risk of suicidal thinking and behavior (suicidality) in children, adolescents, and young adults (ages 18-24) with major depressive disorder (MDD) and other psychiatric disorders. Short-term studies did not show an increase in the risk of suicidality with antidepressants compared to placebo in adults beyond age 24; there was a reduction with antidepressants compared to placebo in adults aged 65 and older.

The pooled analyses of placebo-controlled trials in children and adolescents with MDD, obsessive compulsive disorder (OCD), or other psychiatric disorders included a total of 24 short-term trials of 9 antidepressant drugs in over 4400 patients. The pooled analyses of placebo-controlled trials in adults with MDD or other psychiatric disorders included a total of 295 short-term trials (median duration of 2 months) of 11 antidepressant drugs in over 77,000 patients. There was considerable variation in risk of suicidality among drugs, but a tendency toward an increase in the younger patients for almost all drugs studied. There were differences in absolute risk of suicidality across the different indications, with the highest incidence in MDD. The risk differences (drug vs. placebo), however, were relatively stable within age strata and across indications. These risk differences (drug-placebo difference in the number of cases of suicidality per 1000 patients treated) are provided in Table 1.

TABLE 1
Age Range | Drug-Placebo Difference in Number of Cases of Suicidality per 1000 Patients Treated
 | Increases Compared to Placebo
<18 | 14 additional cases
18-24 | 5 additional cases
 | Decreases Compared to Placebo
25-64 | 1 fewer case
≥65 | 6 fewer cases

No suicides occurred in any of the pediatric trials. There were suicides in the adult trials, but the number was not sufficient to reach any conclusion about drug effect on suicide.

It is unknown whether the suicidality risk extends to longer-term use, i.e., beyond several months. However, there is substantial evidence from placebo-controlled maintenance trials in adults with depression that the use of antidepressants can delay the recurrence of depression.

All patients being treated with antidepressants for any indication should be monitored appropriately and observed closely for clinical worsening, suicidality, and unusual changes in behavior, especially during the initial few months of a course of drug therapy, or at times of dose changes, either increases or decreases.

The following symptoms, anxiety, agitation, panic attacks, insomnia, irritability, hostility, aggressiveness, impulsivity, akathisia (psychomotor restlessness), hypomania, and mania, have been reported in adult and pediatric patients being treated with antidepressants for major depressive disorder as well as for other indications, both psychiatric and nonpsychiatric. Although a causal link between the emergence of such symptoms and either the worsening of depression and/or the emergence of suicidal impulses has not been established, there is concern that such symptoms may represent precursors to emerging suicidality.

Consideration should be given to changing the therapeutic regimen, including possibly discontinuing the medication, in patients whose depression is persistently worse, or who are experiencing emergent suicidality or symptoms that might be precursors to worsening depression or suicidality, especially if these symptoms are severe, abrupt in onset, or were not part of the patient's presenting symptoms.

If the decision has been made to discontinue treatment, medication should be tapered, as rapidly as is feasible, but with recognition that abrupt discontinuation can be associated with certain symptoms [see Dosage and Administration (2.4)].

Families and caregivers of patients being treated with antidepressants for major depressive disorder or other indications, both psychiatric and nonpsychiatric, should be alerted about the need to monitor patients for the emergence of agitation, irritability, unusual changes in behavior, and the other symptoms described above, as well as the emergence of suicidality, and to report such symptoms immediately to health care providers. Such monitoring should include daily observation by families and caregivers [see also Patient Counseling Information (17.1)]. Prescriptions for Lexapro should be written for the smallest quantity of tablets consistent with good patient management, in order to reduce the risk of overdose.

Screening Patients for Bipolar Disorder

A major depressive episode may be the initial presentation of bipolar disorder. It is generally believed (though not established in controlled trials) that treating such an episode with an antidepressant alone may increase the likelihood of precipitation of a mixed/manic episode in patients at risk for bipolar disorder. Whether any of the symptoms described above represent such a conversion is unknown. However, prior to initiating treatment with an antidepressant, patients with depressive symptoms should be adequately screened to determine if they are at risk for bipolar disorder; such screening should include a detailed psychiatric history, including a family history of suicide, bipolar disorder, and depression. It should be noted that Lexapro is not approved for use in treating bipolar depression.

5.2 Serotonin Syndrome

The development of a potentially life-threatening serotonin syndrome has been reported with SNRIs and SSRIs, including Lexapro, alone but particularly with concomitant use of other serotonergic drugs (including triptans, tricyclic antidepressants, fentanyl, lithium, tramadol, tryptophan, buspirone, and St. John's Wort) and with drugs that impair metabolism of serotonin (in particular, MAOIs, both those intended to treat psychiatric disorders and also others, such as linezolid and intravenous methylene blue).

Serotonin syndrome symptoms may include mental status changes (e.g., agitation, hallucinations, delirium, and coma), autonomic instability (e.g., tachycardia, labile blood pressure, dizziness, diaphoresis, flushing, hyperthermia), neuromuscular symptoms (e.g., tremor, rigidity, myoclonus, hyperreflexia, incoordination) seizures, and/or gastrointestinal symptoms (e.g., nausea, vomiting, diarrhea). Patients should be monitored for the emergence of serotonin syndrome.

The concomitant use of Lexapro with MAOIs intended to treat psychiatric disorders is contraindicated. Lexapro should also not be started in a patient who is being treated with MAOIs such as linezolid or intravenous methylene blue. All reports with methylene blue that provided information on the route of administration involved intravenous administration in the dose range of 1 mg/kg to 8 mg/kg. No reports involved the administration of methylene blue by other routes (such as oral tablets or local tissue injection) or at lower doses. There may be circumstances when it is necessary to initiate treatment with an MAOI such as linezolid or intravenous methylene blue in a patient taking Lexapro. Lexapro should be discontinued before initiating treatment with the MAOI [see Contraindications (4.1) and Dosage and Administration (2.5 and 2.6)].

If concomitant use of Lexapro with other serotonergic drugs including, triptans, tricyclic antidepressants, fentanyl, lithium, tramadol, buspirone, tryptophan and St. John's Wort is clinically warranted, patients should be made aware of a potential increased risk for serotonin syndrome, particularly during treatment initiation and dose increases.

Treatment with Lexapro and any concomitant serotonergic agents, should be discontinued immediately if the above events occur and supportive symptomatic treatment should be initiated.

5.3 Discontinuation of Treatment with Lexapro

During marketing of Lexapro and other SSRIs and SNRIs (serotonin and norepinephrine reuptake inhibitors), there have been spontaneous reports of adverse events occurring upon discontinuation of these drugs, particularly when abrupt, including the following: dysphoric mood, irritability, agitation, dizziness, sensory disturbances (e.g., paresthesias such as electric shock sensations), anxiety, confusion, headache, lethargy, emotional lability, insomnia, and hypomania. While these events are generally self-limiting, there have been reports of serious discontinuation symptoms.

Patients should be monitored for these symptoms when discontinuing treatment with Lexapro. A gradual reduction in the dose rather than abrupt cessation is recommended whenever possible. If intolerable symptoms occur following a decrease in the dose or upon discontinuation of treatment, then resuming the previously prescribed dose may be considered. Subsequently, the physician may continue decreasing the dose but at a more gradual rate [see Dosage and Administration (2.4)].

5.4 Seizures

Although anticonvulsant effects of racemic citalopram have been observed in animal studies, Lexapro has not been systematically evaluated in patients with a seizure disorder. These patients were excluded from clinical studies during the product's premarketing testing. In clinical trials of Lexapro, cases of convulsion have been reported in association with Lexapro treatment. Like other drugs effective in the treatment of major depressive disorder, Lexapro should be introduced with care in patients with a history of seizure disorder.

5.5 Activation of Mania/Hypomania

In placebo-controlled trials of Lexapro in major depressive disorder, activation of mania/hypomania was reported in one (0.1%) of 715 patients treated with Lexapro and in none of the 592 patients treated with placebo. One additional case of hypomania has been reported in association with Lexapro treatment. Activation of mania/hypomania has also been reported in a small proportion of patients with major affective disorders treated with racemic citalopram and other marketed drugs effective in the treatment of major depressive disorder. As with all drugs effective in the treatment of major depressive disorder, Lexapro should be used cautiously in patients with a history of mania.

5.6 Hyponatremia

Hyponatremia may occur as a result of treatment with SSRIs and SNRIs, including Lexapro. In many cases, this hyponatremia appears to be the result of the syndrome of inappropriate antidiuretic hormone secretion (SIADH), and was reversible when Lexapro was discontinued. Cases with serum sodium lower than 110 mmol/L have been reported. Elderly patients may be at greater risk of developing hyponatremia with SSRIs and SNRIs. Also, patients taking diuretics or who are otherwise volume depleted may be at greater risk [see Geriatric Use (8.5)]. Discontinuation of Lexapro should be considered in patients with symptomatic hyponatremia and appropriate medical intervention should be instituted.

Signs and symptoms of hyponatremia include headache, difficulty concentrating, memory impairment, confusion, weakness, and unsteadiness, which may lead to falls. Signs and symptoms associated with more severe and/or acute cases have included hallucination, syncope, seizure, coma, respiratory arrest, and death.

5.7 Abnormal Bleeding

SSRIs and SNRIs, including Lexapro, may increase the risk of bleeding events. Concomitant use of aspirin, nonsteroidal anti-inflammatory drugs, warfarin, and other anticoagulants may add to the risk. Case reports and epidemiological studies (case-control and cohort design) have demonstrated an association between use of drugs that interfere with serotonin reuptake and the occurrence of gastrointestinal bleeding. Bleeding events related to SSRIs and SNRIs use have ranged from ecchymoses, hematomas, epistaxis, and petechiae to life-threatening hemorrhages.

Patients should be cautioned about the risk of bleeding associated with the concomitant use of Lexapro and NSAIDs, aspirin, or other drugs that affect coagulation.

5.8 Interference with Cognitive and Motor Performance

In a study in normal volunteers, Lexapro 10 mg/day did not produce impairment of intellectual function or psychomotor performance. Because any psychoactive drug may impair judgment, thinking, or motor skills, however, patients should be cautioned about operating hazardous machinery, including automobiles, until they are reasonably certain that Lexapro therapy does not affect their ability to engage in such activities.

5.9 Use in Patients with Concomitant Illness

Clinical experience with Lexapro in patients with certain concomitant systemic illnesses is limited. Caution is advisable in using Lexapro in patients with diseases or conditions that produce altered metabolism or hemodynamic responses.

Lexapro has not been systematically evaluated in patients with a recent history of myocardial infarction or unstable heart disease. Patients with these diagnoses were generally excluded from clinical studies during the product's premarketing testing.

In subjects with hepatic impairment, clearance of racemic citalopram was decreased and plasma concentrations were increased. The recommended dose of Lexapro in hepatically impaired patients is 10 mg/day [see Dosage and Administration (2.3)].

Because escitalopram is extensively metabolized, excretion of unchanged drug in urine is a minor route of elimination. Until adequate numbers of patients with severe renal impairment have been evaluated during chronic treatment with Lexapro, however, it should be used with caution in such patients [see Dosage and Administration (2.3)].

6 ADVERSE REACTIONS

6.1 Clinical Trials Experience

Because clinical studies are conducted under widely varying conditions, adverse reaction rates observed in the clinical studies of a drug cannot be directly compared to rates in the clinical studies of another drug and may not reflect the rates observed in practice.

Clinical Trial Data Sources

Pediatrics (6 -17 years)

Adverse events were collected in 576 pediatric patients (286 Lexapro, 290 placebo) with major depressive disorder in double-blind placebo-controlled studies. Safety and effectiveness of Lexapro in pediatric patients less than 12 years of age has not been established.

Adults

Adverse events information for Lexapro was collected from 715 patients with major depressive disorder who were exposed to escitalopram and from 592 patients who were exposed to placebo in double-blind, placebo-controlled trials. An additional 284 patients with major depressive disorder were newly exposed to escitalopram in open-label trials. The adverse event information for Lexapro in patients with GAD was collected from 429 patients exposed to escitalopram and from 427 patients exposed to placebo in double-blind, placebo-controlled trials.

Adverse events during exposure were obtained primarily by general inquiry and recorded by clinical investigators using terminology of their own choosing. Consequently, it is not possible to provide a meaningful estimate of the proportion of individuals experiencing adverse events without first grouping similar types of events into a smaller number of standardized event categories. In the tables and tabulations that follow, standard World Health Organization (WHO) terminology has been used to classify reported adverse events.

The stated frequencies of adverse reactions represent the proportion of individuals who experienced, at least once, a treatment-emergent adverse event of the type listed. An event was considered treatment-emergent if it occurred for the first time or worsened while receiving therapy following baseline evaluation.

Adverse Events Associated with Discontinuation of Treatment

Major Depressive Disorder

Pediatrics (6 -17 years)

Adverse events were associated with discontinuation of 3.5% of 286 patients receiving Lexapro and 1% of 290 patients receiving placebo. The most common adverse event (incidence at least 1% for Lexapro and greater than placebo) associated with discontinuation was insomnia (1% Lexapro, 0% placebo).

Adults

Among the 715 depressed patients who received Lexapro in placebo-controlled trials, 6% discontinued treatment due to an adverse event, as compared to 2% of 592 patients receiving placebo. In two fixed-dose studies, the rate of discontinuation for adverse events in patients receiving 10 mg/day Lexapro was not significantly different from the rate of discontinuation for adverse events in patients receiving placebo. The rate of discontinuation for adverse events in patients assigned to a fixed dose of 20 mg/day Lexapro was 10%, which was significantly different from the rate of discontinuation for adverse events in patients receiving 10 mg/day Lexapro (4%) and placebo (3%). Adverse events that were associated with the discontinuation of at least 1% of patients treated with Lexapro, and for which the rate was at least twice that of placebo, were nausea (2%) and ejaculation disorder (2% of male patients).

Generalized Anxiety Disorder

Adults

Among the 429 GAD patients who received Lexapro 10-20 mg/day in placebo-controlled trials, 8% discontinued treatment due to an adverse event, as compared to 4% of 427 patients receiving placebo. Adverse events that were associated with the discontinuation of at least 1% of patients treated with Lexapro, and for which the rate was at least twice the placebo rate, were nausea (2%), insomnia (1%), and fatigue (1%).

Incidence of Adverse Reactions in Placebo-Controlled Clinical Trials

Major Depressive Disorder

Pediatrics (6 -17 years)

The overall profile of adverse reactions in pediatric patients was generally similar to that seen in adult studies, as shown in Table 2. However, the following adverse reactions (excluding those which appear in Table 2 and those for which the coded terms were uninformative or misleading) were reported at an incidence of at least 2% for Lexapro and greater than placebo: back pain, urinary tract infection, vomiting, and nasal congestion.

Adults

The most commonly observed adverse reactions in Lexapro patients (incidence of approximately 5% or greater and approximately twice the incidence in placebo patients) were insomnia, ejaculation disorder (primarily ejaculatory delay), nausea, sweating increased, fatigue, and somnolence.

Table 2 enumerates the incidence, rounded to the nearest percent, of treatment-emergent adverse events that occurred among 715 depressed patients who received Lexapro at doses ranging from 10 to 20 mg/day in placebo-controlled trials. Events included are those occurring in 2% or more of patients treated with Lexapro and for which the incidence in patients treated with Lexapro was greater than the incidence in placebo-treated patients.

TABLE 2 Treatment-Emergent Adverse Reactions observed with a frequency of ≥ 2% and greater than placebo for Major Depressive Disorder
Adverse Reaction | Lexapro | Placebo
 | (N=715) % | (N=592) %
Autonomic Nervous System Disorders
Dry Mouth | 6% | 5%
Sweating Increased | 5% | 2%
Central & Peripheral Nervous System Disorders
Dizziness | 5% | 3%
Gastrointestinal Disorders
Nausea | 15% | 7%
Diarrhea | 8% | 5%
Constipation | 3% | 1%
Indigestion | 3% | 1%
Abdominal Pain | 2% | 1%
General
Influenza-like Symptoms | 5% | 4%
Fatigue | 5% | 2%
Psychiatric Disorders
Insomnia | 9% | 4%
Somnolence | 6% | 2%
Appetite Decreased | 3% | 1%
Libido Decreased | 3% | 1%
Respiratory System Disorders
Rhinitis | 5% | 4%
Sinusitis | 3% | 2%
Urogenital
Ejaculation Disorder^1,2 | 9% | <1%
Impotence^2 | 3% | <1%
Anorgasmia^3 | 2% | <1%
^1Primarily ejaculatory delay.
^2Denominator used was for males only (N=225 Lexapro; N=188 placebo).
^3Denominator used was for females only (N=490 Lexapro; N=404 placebo).

Generalized Anxiety Disorder

Adults

The most commonly observed adverse reactions in Lexapro patients (incidence of approximately 5% or greater and approximately twice the incidence in placebo patients) were nausea, ejaculation disorder (primarily ejaculatory delay), insomnia, fatigue, decreased libido, and anorgasmia.

Table 3 enumerates the incidence, rounded to the nearest percent of treatment-emergent adverse events that occurred among 429 GAD patients who received Lexapro 10 to 20 mg/day in placebo-controlled trials. Events included are those occurring in 2% or more of patients treated with Lexapro and for which the incidence in patients treated with Lexapro was greater than the incidence in placebo-treated patients.

TABLE 3 Treatment-Emergent Adverse Reactions observed with a frequency of ≥ 2% and greater than placebo for Generalized Anxiety Disorder
Adverse Reactions | Lexapro | Placebo
 | (N=429) % | (N=427) %
Autonomic Nervous System Disorders
Dry Mouth | 9% | 5%
Sweating Increased | 4% | 1%
Central & Peripheral Nervous System Disorders
Headache | 24% | 17%
Paresthesia | 2% | 1%
Gastrointestinal Disorders
Nausea | 18% | 8%
Diarrhea | 8% | 6%
Constipation | 5% | 4%
Indigestion | 3% | 2%
Vomiting | 3% | 1%
Abdominal Pain | 2% | 1%
Flatulence | 2% | 1%
Toothache | 2% | 0%
General
Fatigue | 8% | 2%
Influenza-like Symptoms | 5% | 4%
Musculoskeletal System Disorder
Neck/Shoulder Pain | 3% | 1%
Psychiatric Disorders
Somnolence | 13% | 7%
Insomnia | 12% | 6%
Libido Decreased | 7% | 2%
Dreaming Abnormal | 3% | 2%
Appetite Decreased | 3% | 1%
Lethargy | 3% | 1%
Respiratory System Disorders
Yawning | 2% | 1%
Urogenital
Ejaculation Disorder^1,2 | 14% | 2%
Anorgasmia^3 | 6% | <1%
Menstrual Disorder | 2% | 1%
^1Primarily ejaculatory delay.
^2Denominator used was for males only (N=182 Lexapro; N=195 placebo).
^3Denominator used was for females only (N=247 Lexapro; N=232 placebo).

Dose Dependency of Adverse Reactions

The potential dose dependency of common adverse reactions (defined as an incidence rate of ≥5% in either the 10 mg or 20 mg Lexapro groups) was examined on the basis of the combined incidence of adverse reactions in two fixed-dose trials. The overall incidence rates of adverse events in 10 mg Lexapro-treated patients (66%) was similar to that of the placebo-treated patients (61%), while the incidence rate in 20 mg/day Lexapro-treated patients was greater (86%). Table 4 shows common adverse reactions that occurred in the 20 mg/day Lexapro group with an incidence that was approximately twice that of the 10 mg/day Lexapro group and approximately twice that of the placebo group.

TABLE 4 Incidence of Common Adverse Reactions in Patients with Major Depressive Disorder
Adverse Reaction | Placebo | 10 mg/day | 20 mg/day
 | (N=311) | Lexapro | Lexapro
 |  | (N=310) | (N=125)
Insomnia | 4% | 7% | 14%
Diarrhea | 5% | 6% | 14%
Dry Mouth | 3% | 4% | 9%
Somnolence | 1% | 4% | 9%
Dizziness | 2% | 4% | 7%
Sweating Increased | <1% | 3% | 8%
Constipation | 1% | 3% | 6%
Fatigue | 2% | 2% | 6%
Indigestion | 1% | 2% | 6%

Male and Female Sexual Dysfunction with SSRIs

Although changes in sexual desire, sexual performance, and sexual satisfaction often occur as manifestations of a psychiatric disorder, they may also be a consequence of pharmacologic treatment. In particular, some evidence suggests that SSRIs can cause such untoward sexual experiences.

Reliable estimates of the incidence and severity of untoward experiences involving sexual desire, performance, and satisfaction are difficult to obtain, however, in part because patients and physicians may be reluctant to discuss them. Accordingly, estimates of the incidence of untoward sexual experience and performance cited in product labeling are likely to underestimate their actual incidence.

TABLE 5 Incidence of Sexual Side Effects in Placebo-Controlled Clinical Trials
Adverse Event | Lexapro | Placebo
 | In Males Only
 | (N=407) | (N=383)
Ejaculation Disorder (primarily ejaculatory delay) | 12% | 1%
Libido Decreased | 6% | 2%
Impotence | 2% | <1%
 | In Females Only
 | (N=737) | (N=636)
Libido Decreased | 3% | 1%
Anorgasmia | 3% | <1%

There are no adequately designed studies examining sexual dysfunction with escitalopram treatment.

Priapism has been reported with all SSRIs.

While it is difficult to know the precise risk of sexual dysfunction associated with the use of SSRIs, physicians should routinely inquire about such possible side effects.

Vital Sign Changes

Lexapro and placebo groups were compared with respect to (1) mean change from baseline in vital signs (pulse, systolic blood pressure, and diastolic blood pressure) and (2) the incidence of patients meeting criteria for potentially clinically significant changes from baseline in these variables. These analyses did not reveal any clinically important changes in vital signs associated with Lexapro treatment. In addition, a comparison of supine and standing vital sign measures in subjects receiving Lexapro indicated that Lexapro treatment is not associated with orthostatic changes.

Weight Changes

Patients treated with Lexapro in controlled trials did not differ from placebo-treated patients with regard to clinically important change in body weight.

Laboratory Changes

Lexapro and placebo groups were compared with respect to (1) mean change from baseline in various serum chemistry, hematology, and urinalysis variables, and (2) the incidence of patients meeting criteria for potentially clinically significant changes from baseline in these variables. These analyses revealed no clinically important changes in laboratory test parameters associated with Lexapro treatment.

ECG Changes

Electrocardiograms from Lexapro (N=625) and placebo (N=527) groups were compared with respect to outliers defined as subjects with QTc changes over 60 msec from baseline or absolute values over 500 msec post-dose, and subjects with heart rate increases to over 100 bpm or decreases to less than 50 bpm with a 25% change from baseline (tachycardic or bradycardic outliers, respectively). None of the patients in the Lexapro group had a QTcF interval >500 msec or a prolongation >60 msec compared to 0.2% of patients in the placebo group. The incidence of tachycardic outliers was 0.2% in the Lexapro and the placebo group. The incidence of bradycardic outliers was 0.5% in the Lexapro group and 0.2% in the placebo group.

QTcF interval was evaluated in a randomized, placebo and active (moxifloxacin 400 mg) controlled cross-over, escalating multiple-dose study in 113 healthy subjects. The maximum mean (95% upper confidence bound) difference from placebo arm were 4.5 (6.4) and 10.7 (12.7) msec for 10 mg and supratherapeutic 30 mg escitalopram given once daily, respectively. Based on the established exposure-response relationship, the predicted QTcF change from placebo arm (95% confidence interval) under the Cmax for the dose of 20 mg is 6.6 (7.9) msec. Escitalopram 30 mg given once daily resulted in mean Cmax of 1.7-fold higher than the mean Cmax for the maximum recommended therapeutic dose at steady state (20 mg). The exposure under supratherapeutic 30 mg dose is similar to the steady state concentrations expected in CYP2C19 poor metabolizers following a therapeutic dose of 20 mg.

Other Reactions Observed During the Premarketing Evaluation of Lexapro

Following is a list of treatment-emergent adverse events, as defined in the introduction to the ADVERSE REACTIONS section, reported by the 1428 patients treated with Lexapro for periods of up to one year in double-blind or open-label clinical trials during its premarketing evaluation. The listing does not include those events already listed in Tables 2 & 3, those events for which a drug cause was remote and at a rate less than 1% or lower than placebo, those events which were so general as to be uninformative, and those events reported only once which did not have a substantial probability of being acutely life threatening. Events are categorized by body system. Events of major clinical importance are described in the Warnings and Precautions section (5).

Cardiovascular - hypertension, palpitation.

Central and Peripheral Nervous System Disorders - light-headed feeling, migraine.

Gastrointestinal Disorders - abdominal cramp, heartburn, gastroenteritis.

General - allergy, chest pain, fever, hot flushes, pain in limb.

Metabolic and Nutritional Disorders - increased weight.

Musculoskeletal System Disorders - arthralgia, myalgia jaw stiffness.

Psychiatric Disorders - appetite increased, concentration impaired, irritability.

Reproductive Disorders/Female - menstrual cramps, menstrual disorder.

Respiratory System Disorders - bronchitis, coughing, nasal congestion, sinus congestion, sinus headache.

Skin and Appendages Disorders - rash.

Special Senses - vision blurred, tinnitus.

Urinary System Disorders - urinary frequency, urinary tract infection.

6.2 Post-Marketing Experience

Adverse Reactions Reported Subsequent to the Marketing of Escitalopram

The following additional adverse reactions have been identified from spontaneous reports of escitalopram received worldwide. These adverse reactions have been chosen for inclusion because of a combination of seriousness, frequency of reporting, or potential causal connection to escitalopram and have not been listed elsewhere in labeling. However, because these adverse reactions were reported voluntarily from a population of uncertain size, it is not always possible to reliably estimate their frequency or establish a causal relationship to drug exposure. These events include:

Blood and Lymphatic System Disorders: anemia, agranulocytis, aplastic anemia, hemolytic anemia, idiopathic thrombocytopenia purpura, leukopenia, thrombocytopenia.

Cardiac Disorders: atrial fibrillation, bradycardia, cardiac failure, myocardial infarction, tachycardia, torsade de pointes, ventricular arrhythmia, ventricular tachycardia.

Ear and labyrinth disorders: vertigo

Endocrine Disorders: diabetes mellitus, hyperprolactinemia, SIADH.

Eye Disorders: diplopia, glaucoma, mydriasis, visual disturbance.

Gastrointestinal Disorder: dysphagia, gastrointestinal hemorrhage, gastroesophageal reflux, pancreatitis, rectal hemorrhage.

General Disorders and Administration Site Conditions: abnormal gait, asthenia, edema, fall, feeling abnormal, malaise.

Hepatobiliary Disorders: fulminant hepatitis, hepatic failure, hepatic necrosis, hepatitis.

Immune System Disorders: allergic reaction, anaphylaxis.

Investigations: bilirubin increased, decreased weight, electrocardiogram QT prolongation, hepatic enzymes increased,hypercholesterolemia, INR increased, prothrombin decreased.

Metabolism and Nutrition Disorders: hyperglycemia, hypoglycemia, hypokalemia, hyponatremia.

Musculoskeletal and Connective Tissue Disorders: muscle cramp, muscle stiffness, muscle weakness, rhabdomyolysis.

Nervous System Disorders: akathisia, amnesia, ataxia, choreoathetosis, cerebrovascular accident, dysarthria, dyskinesia, dystonia, extrapyramidal disorders, grand mal seizures (or convulsions), hypoaesthesia, myoclonus, nystagmus, Parkinsonism, restless legs, seizures, syncope, tardive dyskinesia, tremor.

Pregnancy, Puerperium and Perinatal Conditions: spontaneous abortion.

Psychiatric Disorders: acute psychosis, aggression, agitation, anger, anxiety, apathy, completed suicide, confusion, depersonalization, depression aggravated, delirium, delusion, disorientation, feeling unreal, hallucinations (visual and auditory), mood swings, nervousness, nightmare, panic reaction, paranoia, restlessness, self-harm or thoughts of self-harm, suicide attempt, suicidal ideation, suicidal tendency.

Renal and Urinary Disorders: acute renal failure, dysuria, urinary retention.

Reproductive System and Breast Disorders: menorrhagia, priapism.

Respiratory, Thoracic and Mediastinal Disorders: dyspnea, epistaxis, pulmonary embolism, pulmonary hypertension of the newborn.

Skin and Subcutaneous Tissue Disorders: alopecia, angioedema, dermatitis, ecchymosis, erythema multiforme, photosensitivity reaction, Stevens Johnson Syndrome, toxic epidermal necrolysis, urticaria.

Vascular Disorders: deep vein thrombosis, flushing, hypertensive crisis, hypotension, orthostatic hypotension, phlebitis, thrombosis.

7 DRUG INTERACTIONS

7.1 Monoamine Oxidase Inhibitors (MAOIs)

[See Dosage and Administration (2.5 and 2.6), Contraindications (4.1) and Warnings and Precautions (5.2)].

7.2 Serotonergic Drugs

[See Dosage and Administration (2.5 and 2.6), Contraindications (4.1) and Warnings and Precautions (5.2)].

7.3 Triptans

There have been rare postmarketing reports of serotonin syndrome with use of an SSRI and a triptan. If concomitant treatment of Lexapro with a triptan is clinically warranted, careful observation of the patient is advised, particularly during treatment initiation and dose increases [see Warnings and Precautions (5.2)].

7.4 CNS Drugs

Given the primary CNS effects of escitalopram, caution should be used when it is taken in combination with other centrally acting drugs.

7.5 Alcohol

Although Lexapro did not potentiate the cognitive and motor effects of alcohol in a clinical trial, as with other psychotropic medications, the use of alcohol by patients taking Lexapro is not recommended.

7.6 Drugs That Interfere With Hemostasis (NSAIDs, Aspirin, Warfarin, etc.)

Serotonin release by platelets plays an important role in hemostasis. Epidemiological studies of the case-control and cohort design that have demonstrated an association between use of psychotropic drugs that interfere with serotonin reuptake and the occurrence of upper gastrointestinal bleeding have also shown that concurrent use of an NSAID or aspirin may potentiate the risk of bleeding. Altered anticoagulant effects, including increased bleeding, have been reported when SSRIs and SNRIs are coadministered with warfarin. Patients receiving warfarin therapy should be carefully monitored when Lexapro is initiated or discontinued.

7.7 Cimetidine

In subjects who had received 21 days of 40 mg/day racemic citalopram, combined administration of 400 mg twice a day cimetidine for 8 days resulted in an increase in citalopram AUC and Cmax of 43% and 39%, respectively. The clinical significance of these findings is unknown.

7.8 Digoxin

In subjects who had received 21 days of 40 mg/day racemic citalopram, combined administration of citalopram and digoxin (single dose of 1 mg) did not significantly affect the pharmacokinetics of either citalopram or digoxin.

7.9 Lithium

Coadministration of racemic citalopram (40 mg/day for 10 days) and lithium (30 mmol/day for 5 days) had no significant effect on the pharmacokinetics of citalopram or lithium. Nevertheless, plasma lithium levels should be monitored with appropriate adjustment to the lithium dose in accordance with standard clinical practice. Because lithium may enhance the serotonergic effects of escitalopram, caution should be exercised when Lexapro and lithium are coadministered.

7.10 Pimozide and Celexa

In a controlled study, a single dose of pimozide 2 mg co-administered with racemic citalopram 40 mg given once daily for 11 days was associated with a mean increase in QTc values of approximately 10 msec compared to pimozide given alone. Racemic citalopram did not alter the mean AUC or Cmax of pimozide. The mechanism of this pharmacodynamic interaction is not known.

7.11 Sumatriptan

There have been rare postmarketing reports describing patients with weakness, hyperreflexia, and incoordination following the use of an SSRI and sumatriptan. If concomitant treatment with sumatriptan and an SSRI (e.g., fluoxetine, fluvoxamine, paroxetine, sertraline, citalopram, escitalopram) is clinically warranted, appropriate observation of the patient is advised.

7.12 Theophylline

Combined administration of racemic citalopram (40 mg/day for 21 days) and the CYP1A2 substrate theophylline (single dose of 300 mg) did not affect the pharmacokinetics of theophylline. The effect of theophylline on the pharmacokinetics of citalopram was not evaluated.

7.13 Warfarin

Administration of 40 mg/day racemic citalopram for 21 days did not affect the pharmacokinetics of warfarin, a CYP3A4 substrate. Prothrombin time was increased by 5%, the clinical significance of which is unknown.

7.14 Carbamazepine

Combined administration of racemic citalopram (40 mg/day for 14 days) and carbamazepine (titrated to 400 mg/day for 35 days) did not significantly affect the pharmacokinetics of carbamazepine, a CYP3A4 substrate. Although trough citalopram plasma levels were unaffected, given the enzyme-inducing properties of carbamazepine, the possibility that carbamazepine might increase the clearance of escitalopram should be considered if the two drugs are coadministered.

7.15 Triazolam

Combined administration of racemic citalopram (titrated to 40 mg/day for 28 days) and the CYP3A4 substrate triazolam (single dose of 0.25 mg) did not significantly affect the pharmacokinetics of either citalopram or triazolam.

7.16 Ketoconazole

Combined administration of racemic citalopram (40 mg) and ketoconazole (200 mg), a potent CYP3A4 inhibitor, decreased the Cmax and AUC of ketoconazole by 21% and 10%, respectively, and did not significantly affect the pharmacokinetics of citalopram.

7.17 Ritonavir

Combined administration of a single dose of ritonavir (600 mg), both a CYP3A4 substrate and a potent inhibitor of CYP3A4, and escitalopram (20 mg) did not affect the pharmacokinetics of either ritonavir or escitalopram.

7.18 CYP3A4 and -2C19 Inhibitors

In vitro studies indicated that CYP3A4 and -2C19 are the primary enzymes involved in the metabolism of escitalopram. However, coadministration of escitalopram (20 mg) and ritonavir (600 mg), a potent inhibitor of CYP3A4, did not significantly affect the pharmacokinetics of escitalopram. Because escitalopram is metabolized by multiple enzyme systems, inhibition of a single enzyme may not appreciably decrease escitalopram clearance.

7.19 Drugs Metabolized by Cytochrome P4502D6

In vitro studies did not reveal an inhibitory effect of escitalopram on CYP2D6. In addition, steady state levels of racemic citalopram were not significantly different in poor metabolizers and extensive CYP2D6 metabolizers after multiple-dose administration of citalopram, suggesting that coadministration, with escitalopram, of a drug that inhibits CYP2D6, is unlikely to have clinically significant effects on escitalopram metabolism. However, there are limited in vivo data suggesting a modest CYP2D6 inhibitory effect for escitalopram, i.e., coadministration of escitalopram (20 mg/day for 21 days) with the tricyclic antidepressant desipramine (single dose of 50 mg), a substrate for CYP2D6, resulted in a 40% increase in Cmax and a 100% increase in AUC of desipramine. The clinical significance of this finding is unknown. Nevertheless, caution is indicated in the coadministration of escitalopram and drugs metabolized by CYP2D6.

7.20 Metoprolol

Administration of 20 mg/day Lexapro for 21 days in healthy volunteers resulted in a 50% increase in Cmax and 82% increase in AUC of the beta-adrenergic blocker metoprolol (given in a single dose of 100 mg). Increased metoprolol plasma levels have been associated with decreased cardioselectivity. Coadministration of Lexapro and metoprolol had no clinically significant effects on blood pressure or heart rate.

7.21 Electroconvulsive Therapy (ECT)

There are no clinical studies of the combined use of ECT and escitalopram.

8 USE IN SPECIFIC POPULATIONS

8.1 Pregnancy

Pregnancy Category C

In a rat embryo/fetal development study, oral administration of escitalopram (56, 112, or 150 mg/kg/day) to pregnant animals during the period of organogenesis resulted in decreased fetal body weight and associated delays in ossification at the two higher doses (approximately ≥ 56 times the maximum recommended human dose [MRHD] of 20 mg/day on a body surface area [mg/m^2] basis). Maternal toxicity (clinical signs and decreased body weight gain and food consumption), mild at 56 mg/kg/day, was present at all dose levels. The developmental no-effect dose of 56 mg/kg/day is approximately 28 times the MRHD on a mg/m^2 basis. No teratogenicity was observed at any of the doses tested (as high as 75 times the MRHD on a mg/m^2 basis).

When female rats were treated with escitalopram (6, 12, 24, or 48 mg/kg/day) during pregnancy and through weaning, slightly increased offspring mortality and growth retardation were noted at 48 mg/kg/day which is approximately 24 times the MRHD on a mg/m^2 basis. Slight maternal toxicity (clinical signs and decreased body weight gain and food consumption) was seen at this dose. Slightly increased offspring mortality was also seen at 24 mg/kg/day. The no-effect dose was 12 mg/kg/day which is approximately 6 times the MRHD on a mg/m^2 basis.

In animal reproduction studies, racemic citalopram has been shown to have adverse effects on embryo/fetal and postnatal development, including teratogenic effects, when administered at doses greater than human therapeutic doses.

In two rat embryo/fetal development studies, oral administration of racemic citalopram (32, 56, or 112 mg/kg/day) to pregnant animals during the period of organogenesis resulted in decreased embryo/fetal growth and survival and an increased incidence of fetal abnormalities (including cardiovascular and skeletal defects) at the high dose. This dose was also associated with maternal toxicity (clinical signs, decreased body weight gain). The developmental no-effect dose was 56 mg/kg/day. In a rabbit study, no adverse effects on embryo/fetal development were observed at doses of racemic citalopram of up to 16 mg/kg/day. Thus, teratogenic effects of racemic citalopram were observed at a maternally toxic dose in the rat and were not observed in the rabbit.

When female rats were treated with racemic citalopram (4.8, 12.8, or 32 mg/kg/day) from late gestation through weaning, increased offspring mortality during the first 4 days after birth and persistent offspring growth retardation were observed at the highest dose. The no-effect dose was 12.8 mg/kg/day. Similar effects on offspring mortality and growth were seen when dams were treated throughout gestation and early lactation at doses ≥ 24 mg/kg/day. A no-effect dose was not determined in that study.

There are no adequate and well-controlled studies in pregnant women; therefore, escitalopram should be used during pregnancy only if the potential benefit justifies the potential risk to the fetus.

Pregnancy-Nonteratogenic Effects

Neonates exposed to Lexapro and other SSRIs or serotonin and norepinephrine reuptake inhibitors (SNRIs), late in the third trimester have developed complications requiring prolonged hospitalization, respiratory support, and tube feeding. Such complications can arise immediately upon delivery. Reported clinical findings have included respiratory distress, cyanosis, apnea, seizures, temperature instability, feeding difficulty, vomiting, hypoglycemia, hypotonia, hypertonia, hyperreflexia, tremor, jitteriness, irritability, and constant crying. These features are consistent with either a direct toxic effect of SSRIs and SNRIs or, possibly, a drug discontinuation syndrome. It should be noted that, in some cases, the clinical picture is consistent with serotonin syndrome [see Warnings and Precautions (5.2)].

Infants exposed to SSRIs in pregnancy may have an increased risk for persistent pulmonary hypertension of the newborn (PPHN). PPHN occurs in 1 - 2 per 1,000 live births in the general population and is associated with substantial neonatal morbidity and mortality. Several recent epidemiologic studies suggest a positive statistical association between SSRI use (including Lexapro) in pregnancy and PPHN. Other studies do not show a significant statistical association.

Physicians should also note the results of a prospective longitudinal study of 201 pregnant women with a history of major depression, who were either on antidepressants or had received antidepressants less than 12 weeks prior to their last menstrual period, and were in remission. Women who discontinued antidepressant medication during pregnancy showed a significant increase in relapse of their major depression compared to those women who remained on antidepressant medication throughout pregnancy.

When treating a pregnant woman with Lexapro, the physician should carefully consider both the potential risks of taking an SSRl, along with the established benefits of treating depression with an antidepressant. This decision can only be made on a case by case basis [see Dosage and Administration (2.1.)].

8.2 Labor and Delivery

The effect of Lexapro on labor and delivery in humans is unknown.

8.3 Nursing Mothers

Escitalopram is excreted in human breast milk. Limited data from women taking 10-20 mg escitalopram showed that exclusively breast-fed infants receive approximately 3.9% of the maternal weight-adjusted dose of escitalopram and 1.7% of the maternal weight-adjusted dose of desmethylcitalopram. There were two reports of infants experiencing excessive somnolence, decreased feeding, and weight loss in association with breastfeeding from a racemic citalopram-treated mother; in one case, the infant was reported to recover completely upon discontinuation of racemic citalopram by its mother and, in the second case, no follow-up information was available. Caution should be exercised and breastfeeding infants should be observed for adverse reactions when Lexapro is administered to a nursing woman.

8.4 Pediatric Use

Safety and effectiveness of Lexapro has not been established in pediatric patients (less than 12 years of age) with Major Depressive Disorder. Safety and effectiveness of Lexapro has been established in adolescents (12 to 17 years of age) for the treatment of major depressive disorder [see Clinical Studies (14.1)]. Although maintenance efficacy in adolescent patients with Major Depressive Disorder has not been systematically evaluated, maintenance efficacy can be extrapolated from adult data along with comparisons of escitalopram pharmacokinetic parameters in adults and adolescent patients.

Safety and effectiveness of Lexapro has not been established in pediatric patients less than 18 years of age with Generalized Anxiety Disorder.

Decrease appetite and weight loss have been observed in association with the use of SSRIs. Consequently, regular monitoring of weight and growth should be performed in children and adolescents treated with an SSRI such as Lexapro.

8.5 Geriatric Use

Approximately 6% of the 1144 patients receiving escitalopram in controlled trials of Lexapro in major depressive disorder and GAD were 60 years of age or older; elderly patients in these trials received daily doses of Lexapro between 10 and 20 mg. The number of elderly patients in these trials was insufficient to adequately assess for possible differential efficacy and safety measures on the basis of age. Nevertheless, greater sensitivity of some elderly individuals to effects of Lexapro cannot be ruled out.

SSRIs and SNRIs, including Lexapro, have been associated with cases of clinically significant hyponatremia in elderly patients, who may be at greater risk for this adverse event [see Hyponatremia (5.6)].

In two pharmacokinetic studies, escitalopram half-life was increased by approximately 50% in elderly subjects as compared to young subjects and Cmax was unchanged [see Clinical Pharmacology (12.3)]. 10 mg/day is the recommended dose for elderly patients [see Dosage and Administration (2.3)].

Of 4422 patients in clinical studies of racemic citalopram, 1357 were 60 and over, 1034 were 65 and over, and 457 were 75 and over. No overall differences in safety or effectiveness were observed between these subjects and younger subjects, and other reported clinical experience has not identified differences in responses between the elderly and younger patients, but again, greater sensitivity of some elderly individuals cannot be ruled out.

9 DRUG ABUSE AND DEPENDENCE

9.2 Abuse and Dependence

Physical and Psychological Dependence

Animal studies suggest that the abuse liability of racemic citalopram is low. Lexapro has not been systematically studied in humans for its potential for abuse, tolerance, or physical dependence. The premarketing clinical experience with Lexapro did not reveal any drug-seeking behavior. However, these observations were not systematic and it is not possible to predict on the basis of this limited experience the extent to which a CNS-active drug will be misused, diverted, and/or abused once marketed. Consequently, physicians should carefully evaluate Lexapro patients for history of drug abuse and follow such patients closely, observing them for signs of misuse or abuse (e.g., development of tolerance, incrementations of dose, drug-seeking behavior).

10 OVERDOSAGE

10.1 Human Experience

In clinical trials of escitalopram, there were reports of escitalopram overdose, including overdoses of up to 600 mg, with no associated fatalities. During the postmarketing evaluation of escitalopram, Lexapro overdoses involving overdoses of over 1000 mg have been reported. As with other SSRIs, a fatal outcome in a patient who has taken an overdose of escitalopram has been rarely reported.

Symptoms most often accompanying escitalopram overdose, alone or in combination with other drugs and/or alcohol, included convulsions, coma, dizziness, hypotension, insomnia, nausea, vomiting, sinus tachycardia, somnolence, and ECG changes (including QT prolongation and very rare cases of torsade de pointes). Acute renal failure has been very rarely reported accompanying overdose.

10.2 Management of Overdose

Establish and maintain an airway to ensure adequate ventilation and oxygenation. Gastric evacuation by lavage and use of activated charcoal should be considered. Careful observation and cardiac and vital sign monitoring are recommended, along with general symptomatic and supportive care. Due to the large volume of distribution of escitalopram, forced diuresis, dialysis, hemoperfusion, and exchange transfusion are unlikely to be of benefit. There are no specific antidotes for Lexapro.

In managing overdosage, consider the possibility of multiple-drug involvement. The physician should consider contacting a poison control center for additional information on the treatment of any overdose.

11 DESCRIPTION

Lexapro® (escitalopram oxalate) is an orally administered selective serotonin reuptake inhibitor (SSRI). Escitalopram is the pure S-enantiomer (single isomer) of the racemic bicyclic phthalane derivative citalopram. Escitalopram oxalate is designated S-(+)-1-[3-(dimethyl-amino)propyl]-1-(p-fluorophenyl)-5-phthalancarbonitrile oxalate with the following structural formula:

The molecular formula is C20H21FN2O • C2H2O4 and the molecular weight is 414.40.

Escitalopram oxalate occurs as a fine, white to slightly-yellow powder and is freely soluble in methanol and dimethyl sulfoxide (DMSO), soluble in isotonic saline solution, sparingly soluble in water and ethanol, slightly soluble in ethyl acetate, and insoluble in heptane.

Lexapro (escitalopram oxalate) is available as tablets or as an oral solution.

Lexapro tablets are film-coated, round tablets containing escitalopram oxalate in strengths equivalent to 5 mg, 10 mg, and 20 mg escitalopram base. The 10 and 20 mg tablets are scored. The tablets also contain the following inactive ingredients: talc, croscarmellose sodium, microcrystalline cellulose/colloidal silicon dioxide, and magnesium stearate. The film coating contains hypromellose, titanium dioxide, and polyethylene glycol.

Lexapro oral solution contains escitalopram oxalate equivalent to 1 mg/mL escitalopram base. It also contains the following inactive ingredients: sorbitol, purified water, citric acid, sodium citrate, malic acid, glycerin, propylene glycol, methylparaben, propylparaben, and natural peppermint flavor.

12 CLINICAL PHARMACOLOGY

12.1 Mechanism of Action

The mechanism of antidepressant action of escitalopram, the S-enantiomer of racemic citalopram, is presumed to be linked to potentiation of serotonergic activity in the central nervous system (CNS) resulting from its inhibition of CNS neuronal reuptake of serotonin (5-HT).

12.2 Pharmacodynamics

In vitro and in vivo studies in animals suggest that escitalopram is a highly selective serotonin reuptake inhibitor (SSRI) with minimal effects on norepinephrine and dopamine neuronal reuptake. Escitalopram is at least 100-fold more potent than the R-enantiomer with respect to inhibition of 5-HT reuptake and inhibition of 5-HT neuronal firing rate. Tolerance to a model of antidepressant effect in rats was not induced by long-term (up to 5 weeks) treatment with escitalopram. Escitalopram has no or very low affinity for serotonergic (5-HT1-7) or other receptors including alpha- and beta-adrenergic, dopamine (D1-5), histamine (H1-3), muscarinic (M1-5), and benzodiazepine receptors. Escitalopram also does not bind to, or has low affinity for, various ion channels including Na^+, K^+, Cl^-, and Ca^++ channels. Antagonism of muscarinic, histaminergic, and adrenergic receptors has been hypothesized to be associated with various anticholinergic, sedative, and cardiovascular side effects of other psychotropic drugs.

12.3 Pharmacokinetics

The single- and multiple-dose pharmacokinetics of escitalopram are linear and dose-proportional in a dose range of 10 to 30 mg/day. Biotransformation of escitalopram is mainly hepatic, with a mean terminal half-life of about 27-32 hours. With once-daily dosing, steady state plasma concentrations are achieved within approximately one week. At steady state, the extent of accumulation of escitalopram in plasma in young healthy subjects was 2.2-2.5 times the plasma concentrations observed after a single dose. The tablet and the oral solution dosage forms of escitalopram oxalate are bioequivalent.

Absorption and Distribution

Following a single oral dose (20 mg tablet or solution) of escitalopram, peak blood levels occur at about 5 hours. Absorption of escitalopram is not affected by food.

The absolute bioavailability of citalopram is about 80% relative to an intravenous dose, and the volume of distribution of citalopram is about 12 L/kg. Data specific on escitalopram are unavailable.

The binding of escitalopram to human plasma proteins is approximately 56%.

Metabolism and Elimination

Following oral administrations of escitalopram, the fraction of drug recovered in the urine as escitalopram and S-demethylcitalopram (S-DCT) is about 8% and 10%, respectively. The oral clearance of escitalopram is 600 mL/min, with approximately 7% of that due to renal clearance.

Escitalopram is metabolized to S-DCT and S-didemethylcitalopram (S-DDCT). In humans, unchanged escitalopram is the predominant compound in plasma. At steady state, the concentration of the escitalopram metabolite S-DCT in plasma is approximately one-third that of escitalopram. The level of S-DDCT was not detectable in most subjects. In vitro studies show that escitalopram is at least 7 and 27 times more potent than S-DCT and S-DDCT, respectively, in the inhibition of serotonin reuptake, suggesting that the metabolites of escitalopram do not contribute significantly to the antidepressant actions of escitalopram. S-DCT and S-DDCT also have no or very low affinity for serotonergic (5-HT1-7) or other receptors including alpha- and beta-adrenergic, dopamine (D1-5), histamine (H1-3), muscarinic (M1-5), and benzodiazepine receptors. S-DCT and S-DDCT also do not bind to various ion channels including Na^+, K^+, Cl^-, and Ca^++ channels.

In vitro studies using human liver microsomes indicated that CYP3A4 and CYP2C19 are the primary isozymes involved in the N-demethylation of escitalopram.

Population Subgroups

Age

Adolescents - In a single dose study of 10 mg escitalopram, AUC of escitalopram decreased by 19%, and Cmax increased by 26% in healthy adolescent subjects (12 to 17 years of age) compared to adults. Following multiple dosing of 40 mg/day citalopram, escitalopram elimination half-life, steady-state Cmax and AUC were similar in patients with MDD (12 to 17 years of age) compared to adult patients. No adjustment of dosage is needed in adolescent patients.

Elderly - Escitalopram pharmacokinetics in subjects ≥ 65 years of age were compared to younger subjects in a single-dose and a multiple-dose study. Escitalopram AUC and half-life were increased by approximately 50% in elderly subjects, and Cmax was unchanged. 10 mg is the recommended dose for elderly patients [see Dosage and Administration (2.3)].

Gender - Based on data from single- and multiple-dose studies measuring escitalopram in elderly, young adults, and adolescents, no dosage adjustment on the basis of gender is needed.

Reduced hepatic function - Citalopram oral clearance was reduced by 37% and half-life was doubled in patients with reduced hepatic function compared to normal subjects. 10 mg is the recommended dose of escitalopram for most hepatically impaired patients [see Dosage and Administration (2.3)].

Reduced renal function - In patients with mild to moderate renal function impairment, oral clearance of citalopram was reduced by 17% compared to normal subjects. No adjustment of dosage for such patients is recommended. No information is available about the pharmacokinetics of escitalopram in patients with severely reduced renal function (creatinine clearance < 20 mL/min).

Drug-Drug Interactions

In vitro enzyme inhibition data did not reveal an inhibitory effect of escitalopram on CYP3A4, -1A2, -2C9, -2C19, and -2E1. Based on in vitro data, escitalopram would be expected to have little inhibitory effect on in vivo metabolism mediated by these cytochromes. While in vivo data to address this question are limited, results from drug interaction studies suggest that escitalopram, at a dose of 20 mg, has no 3A4 inhibitory effect and a modest 2D6 inhibitory effect. See Drug Interactions (7.18) for more detailed information on available drug interaction data.

13 NONCLINICAL TOXICOLOGY

13.1 Carcinogenesis, Mutagenesis, Impairment of Fertility

Carcinogenesis

Racemic citalopram was administered in the diet to NMRI/BOM strain mice and COBS WI strain rats for 18 and 24 months, respectively. There was no evidence for carcinogenicity of racemic citalopram in mice receiving up to 240 mg/kg/day. There was an increased incidence of small intestine carcinoma in rats receiving 8 or 24 mg/kg/day racemic citalopram. A no-effect dose for this finding was not established. The relevance of these findings to humans is unknown.

Mutagenesis

Racemic citalopram was mutagenic in the in vitro bacterial reverse mutation assay (Ames test) in 2 of 5 bacterial strains (Salmonella TA98 and TA1537) in the absence of metabolic activation. It was clastogenic in the in vitro Chinese hamster lung cell assay for chromosomal aberrations in the presence and absence of metabolic activation. Racemic citalopram was not mutagenic in the in vitro mammalian forward gene mutation assay (HPRT) in mouse lymphoma cells or in a coupled in vitro/in vivo unscheduled DNA synthesis (UDS) assay in rat liver. It was not clastogenic in the in vitro chromosomal aberration assay in human lymphocytes or in two in vivo mouse micronucleus assays.

Impairment of Fertility

When racemic citalopram was administered orally to 16 male and 24 female rats prior to and throughout mating and gestation at doses of 32, 48, and 72 mg/kg/day, mating was decreased at all doses, and fertility was decreased at doses ≥ 32 mg/kg/day. Gestation duration was increased at 48 mg/kg/day.

13.2 Animal Toxicology and/or Pharmacology

Retinal Changes in Rats

Pathologic changes (degeneration/atrophy) were observed in the retinas of albino rats in the 2-year carcinogenicity study with racemic citalopram. There was an increase in both incidence and severity of retinal pathology in both male and female rats receiving 80 mg/kg/day. Similar findings were not present in rats receiving 24 mg/kg/day of racemic citalopram for two years, in mice receiving up to 240 mg/kg/day of racemic citalopram for 18 months, or in dogs receiving up to 20 mg/kg/day of racemic citalopram for one year.

Additional studies to investigate the mechanism for this pathology have not been performed, and the potential significance of this effect in humans has not been established.

Cardiovascular Changes in Dogs

In a one-year toxicology study, 5 of 10 beagle dogs receiving oral racemic citalopram doses of 8 mg/kg/day died suddenly between weeks 17 and 31 following initiation of treatment. Sudden deaths were not observed in rats at doses of racemic citalopram up to 120 mg/kg/day, which produced plasma levels of citalopram and its metabolites demethylcitalopram and didemethylcitalopram (DDCT) similar to those observed in dogs at 8 mg/kg/day. A subsequent intravenous dosing study demonstrated that in beagle dogs, racemic DDCT caused QT prolongation, a known risk factor for the observed outcome in dogs.

14 CLINICAL STUDIES

14.1 Major Depressive Disorder

Adolescents

The efficacy of Lexapro as an acute treatment for major depressive disorder in adolescent patients was established in an 8-week, flexible-dose, placebo-controlled study that compared Lexapro 10-20 mg/day to placebo in outpatients 12 to 17 years of age inclusive who met DSM-IV criteria for major depressive disorder. The primary outcome was change from baseline to endpoint in the Children's Depression Rating Scale - Revised (CDRS-R). In this study, Lexapro showed statistically significant greater mean improvement compared to placebo on the CDRS-R.

The efficacy of Lexapro in the acute treatment of major depressive disorder in adolescents was established, in part, on the basis of extrapolation from the 8-week, flexible-dose, placebo-controlled study with racemic citalopram 20-40 mg/day. In this outpatient study in children and adolescents 7 to 17 years of age who met DSM-IV criteria for major depressive disorder, citalopram treatment showed statistically significant greater mean improvement from baseline, compared to placebo, on the CDRS-R; the positive results for this trial largely came from the adolescent subgroup.

Two additional flexible-dose, placebo-controlled MDD studies (one Lexapro study in patients ages 7 to 17 and one citalopram study in adolescents) did not demonstrate efficacy.

Although maintenance efficacy in adolescent patients has not been systematically evaluated, maintenance efficacy can be extrapolated from adult data along with comparisons of escitalopram pharmacokinetic parameters in adults and adolescent patients.

Adults

The efficacy of Lexapro as a treatment for major depressive disorder was established in three, 8-week, placebo-controlled studies conducted in outpatients between 18 and 65 years of age who met DSM-IV criteria for major depressive disorder. The primary outcome in all three studies was change from baseline to endpoint in the Montgomery Asberg Depression Rating Scale (MADRS).

A fixed-dose study compared 10 mg/day Lexapro and 20 mg/day Lexapro to placebo and 40 mg/day citalopram. The 10 mg/day and 20 mg/day Lexapro treatment groups showed statistically significant greater mean improvement compared to placebo on the MADRS. The 10 mg and 20 mg Lexapro groups were similar on this outcome measure.

In a second fixed-dose study of 10 mg/day Lexapro and placebo, the 10 mg/day Lexapro treatment group showed statistically significant greater mean improvement compared to placebo on the MADRS.

In a flexible-dose study, comparing Lexapro, titrated between 10 and 20 mg/day, to placebo and citalopram, titrated between 20 and 40 mg/day, the Lexapro treatment group showed statistically significant greater mean improvement compared to placebo on the MADRS.

Analyses of the relationship between treatment outcome and age, gender, and race did not suggest any differential responsiveness on the basis of these patient characteristics.

In a longer-term trial, 274 patients meeting (DSM-IV) criteria for major depressive disorder, who had responded during an initial 8-week, open-label treatment phase with Lexapro 10 or 20 mg/day, were randomized to continuation of Lexapro at their same dose, or to placebo, for up to 36 weeks of observation for relapse. Response during the open-label phase was defined by having a decrease of the MADRS total score to ≤ 12. Relapse during the double-blind phase was defined as an increase of the MADRS total score to ≥ 22, or discontinuation due to insufficient clinical response. Patients receiving continued Lexapro experienced a statistically significant longer time to relapse compared to those receiving placebo.

14.2 Generalized Anxiety Disorder

The efficacy of Lexapro in the acute treatment of Generalized Anxiety Disorder (GAD) was demonstrated in three, 8-week, multicenter, flexible-dose, placebo-controlled studies that compared Lexapro 10-20 mg/day to placebo in adult outpatients between 18 and 80 years of age who met DSM-IV criteria for GAD. In all three studies, Lexapro showed statistically significant greater mean improvement compared to placebo on the Hamilton Anxiety Scale (HAM-A).

There were too few patients in differing ethnic and age groups to adequately assess whether or not Lexapro has differential effects in these groups. There was no difference in response to Lexapro between men and women.

16 HOW SUPPLIED/STORAGE AND HANDLING

16.1 Tablets

10 mg Tablets:
Bottle of 30 NDC # 33261-0699-30

White to off-white, round, scored, film-coated. Imprint on scored side with "F" on the left side and "L" on the right side. Imprint on the non-scored side with "10".

20 mg Tablets:
Bottle of 30 NDC # 33261-0686-30

White to off-white, round, scored, film-coated. Imprint on scored side with "F" on the left side and "L" on the right side. Imprint on the non-scored side with "20".

Storage and Handling

Store at 25°C (77°F); excursions permitted to 15 - 30°C (59-86°F).

17 PATIENT COUNSELING INFORMATION

See FDA-approved Medication Guide

17.1 Information for Patients

Physicians are advised to discuss the following issues with patients for whom they prescribe Lexapro.

General Information about Medication Guide

Prescribers or other health professionals should inform patients, their families, and their caregivers about the benefits and risks associated with treatment with Lexapro and should counsel them in its appropriate use. A patient Medication Guide about “Antidepressant Medicines, Depression and other Serious Mental Illness, and Suicidal Thoughts or Actions” is available for Lexapro. The prescriber or health professional should instruct patients, their families, and their caregivers to read the Medication Guide and should assist them in understanding its contents. Patients should be given the opportunity to discuss the contents of the Medication Guide and to obtain answers to any questions they may have. The complete text of the Medication Guide is reprinted at the end of this document.

Patients should be advised of the following issues and asked to alert their prescriber if these occur while taking Lexapro.

Clinical Worsening and Suicide Risk

Patients, their families, and their caregivers should be encouraged to be alert to the emergence of anxiety, agitation, panic attacks, insomnia, irritability, hostility, aggressiveness, impulsivity, akathisia (psychomotor restlessness), hypomania, mania, other unusual changes in behavior, worsening of depression, and suicidal ideation, especially early during antidepressant treatment and when the dose is adjusted up or down. Families and caregivers of patients should be advised to look for the emergence of such symptoms on a day-to-day basis, since changes may be abrupt. Such symptoms should be reported to the patient's prescriber or health professional, especially if they are severe, abrupt in onset, or were not part of the patient's presenting symptoms. Symptoms such as these may be associated with an increased risk for suicidal thinking and behavior and indicate a need for very close monitoring and possibly changes in the medication [see Warnings and Precautions (5.1)].

Serotonin Syndrome

Patients should be cautioned about the risk of serotonin syndrome with the concomitant use of Lexapro with other serotonergic drugs including triptans, tricyclic antidepressants, fentanyl, lithium, tramadol, tryptophan, buspirone and St. John's Wort, and with drugs that impair metabolism of serotonin (in particular, MAOIs, both those intended to treat psychiatric disorders and also others, such as linezolid) [see Warnings and Precautions (5.2)].

Abnormal Bleeding

Patients should be cautioned about the concomitant use of Lexapro and NSAIDs, aspirin, warfarin, or other drugs that affect coagulation since combined use of psychotropic drugs that interfere with serotonin reuptake and these agents has been associated with an increased risk of bleeding [see Warnings and Precautions (5.7)].

Concomitant Medications

Since escitalopram is the active isomer of racemic citalopram (Celexa), the two agents should not be coadministered. Patients should be advised to inform their physician if they are taking, or plan to take, any prescription or over-the-counter drugs, as there is a potential for interactions.

Continuing the Therapy Prescribed

While patients may notice improvement with Lexapro therapy in 1 to 4 weeks, they should be advised to continue therapy as directed.

Interference with Psychomotor Performance

Because psychoactive drugs may impair judgment, thinking, or motor skills, patients should be cautioned about operating hazardous machinery, including automobiles, until they are reasonably certain that Lexapro therapy does not affect their ability to engage in such activities.

Alcohol

Patients should be told that, although Lexapro has not been shown in experiments with normal subjects to increase the mental and motor skill impairments caused by alcohol, the concomitant use of Lexapro and alcohol in depressed patients is not advised.

Pregnancy and Breast Feeding

Patients should be advised to notify their physician if they

- become pregnant or intend to become pregnant during therapy.
- are breastfeeding an infant.

Need for Comprehensive Treatment Program

Lexapro is indicated as an integral part of a total treatment program for MDD that may include other measures (psychological, educational, social) for patients with this syndrome. Drug treatment may not be indicated for all adolescents with this syndrome. Safety and effectiveness of Lexapro in MDD has not been established in pediatric patients less than 12 years of age. Antidepressants are not intended for use in the adolescent who exhibits symptoms secondary to environmental factors and/or other primary psychiatric disorders. Appropriate educational placement is essential and psychosocial intervention is often helpful. When remedial measures alone are insufficient, the decision to prescribe antidepressant medication will depend upon the physician's assessment of the chronicity and severity of the patient's symptoms.

FDA-Approved Medication Guide

Medication Guide

Lexapro (leks-a-pro)
(escitalopram oxalate)
Tablets/Oral Solution

Read the Medication Guide that comes with Lexapro before you start taking it and each time you get a refill. There may be new information. This Medication Guide does not take the place of talking to your healthcare provider about your medical condition or treatment. Talk with your healthcare provider if there is something you do not understand or want to learn more about.

What is the most important information I should know about Lexapro?

Lexapro and other antidepressant medicines may cause serious side effects, including:

1. Suicidal thoughts or actions:

- Lexapro and other antidepressant medicines may increase suicidal thoughts or actions in some children, teenagers, or young adults within the first few months of treatment or when the dose is changed.
- Depression or other serious mental illnesses are the most important causes of suicidal thoughts or actions.
- Watch for these changes and call your healthcare provider right away if you notice:
  - New or sudden changes in mood, behavior, actions, thoughts, or feelings, especially if severe.
  - Pay particular attention to such changes when Lexapro is started or when the dose is changed.

Keep all follow-up visits with your healthcare provider and call between visits if you are worried about symptoms.

Call your healthcare provider right away if you have any of the following symptoms, or call 911 if an emergency, especially if they are new, worse, or worry you:

- attempts to commit suicide
- acting on dangerous impulses
- acting aggressive or violent
- thoughts about suicide or dying
- new or worse depression
- new or worse anxiety or panic attacks
- feeling agitated, restless, angry or irritable
- trouble sleeping
- an increase in activity or talking more than what is normal for you
- other unusual changes in behavior or mood

Call your healthcare provider right away if you have any of the following symptoms, or call 911 if an emergency. Lexapro may be associated with these serious side effects:

2. Serotonin Syndrome. This condition can be life-threatening and may include:

- agitation, hallucinations, coma or other changes in mental status
- coordination problems or muscle twitching (overactive reflexes)
- racing heartbeat, high or low blood pressure
- sweating or fever
- nausea, vomiting, or diarrhea
- muscle rigidity

3. Severe allergic reactions:

- trouble breathing
- swelling of the face, tongue, eyes or mouth
- rash, itchy welts (hives) or blisters, alone or with fever or joint pain

4. Abnormal bleeding: Lexapro and other antidepressant medicines may increase your risk of bleeding or bruising, especially if you take the blood thinner warfarin (Coumadin®, Jantoven®), a non-steroidal anti-inflammatory drug (NSAIDs, like ibuprofen or naproxen), or aspirin.

5. Seizures or convulsions

6. Manic episodes:

- greatly increased energy
- severe trouble sleeping
- racing thoughts
- reckless behavior
- unusually grand ideas
- excessive happiness or irritability
- talking more or faster than usual

7. Changes in appetite or weight. Children and adolescents should have height and weight monitored during treatment.

8. Low salt (sodium) levels in the blood. Elderly people may be at greater risk for this. Symptoms may include:

- headache
- weakness or feeling unsteady
- confusion, problems concentrating or thinking or memory problems

Do not stop Lexapro without first talking to your healthcare provider. Stopping Lexapro too quickly may cause serious symptoms including:

- anxiety, irritability, high or low mood, feeling restless or changes in sleep habits
- headache, sweating, nausea, dizziness
- electric shock-like sensations, shaking, confusion

What is Lexapro?

Lexapro is a prescription medicine used to treat depression. It is important to talk with your healthcare provider about the risks of treating depression and also the risks of not treating it. You should discuss all treatment choices with your healthcare provider. Lexapro is also used to treat:

- Major Depressive Disorder (MDD)
- Generalized Anxiety Disorder (GAD)

Talk to your healthcare provider if you do not think that your condition is getting better with Lexapro treatment.

Who should not take Lexapro?

Do not take Lexapro if you:

- are allergic to escitalopram oxalate or citalopram hydrobromide or any of the ingredients in Lexapro. See the end of this Medication Guide for a complete list of ingredients in Lexapro.
- take a monoamine oxidase inhibitor (MAOI). Ask your healthcare provider or pharmacist if you are not sure if you take an MAOI, including the antibiotic linezolid.
- Do not take an MAOI within 2 weeks of stopping Lexapro unless directed to do so by your physician.
- Do not start Lexapro if you stopped taking an MAOI in the last 2 weeks unless directed to do so by your physician.
  People who take Lexapro close in time to an MAOI may have serious or even life-threatening side effects. Get medical help right away if you have any of these symptoms:
  - high fever
  - uncontrolled muscle spasms
  - stiff muscles
  - rapid changes in heart rate or blood pressure
  - confusion
  - loss of consciousness (pass out)
- take the antipsychotic medicine pimozide (Orap®) because taking this drug with Lexapro can cause serious heart problems.

What should I tell my healthcare provider before taking Lexapro? Ask if you are not sure.

Before starting Lexapro, tell your healthcare provider if you:

- Are taking certain drugs such as:
  - Triptans used to treat migraine headache
  - Medicines used to treat mood, anxiety, psychotic or thought disorders, including tricyclics, lithium, SSRIs, SNRIs, or antipsychotics
  - tramadol
  - Over-the-counter supplements such as tryptophan or St. John's Wort
- have liver problems
- have kidney problems
- have heart problems
- have or had seizures or convulsions
- have bipolar disorder or mania
- have low sodium levels in your blood
- have a history of a stroke
- have high blood pressure
- have or had bleeding problems
- are pregnant or plan to become pregnant. It is not known if Lexapro will harm your unborn baby. Talk to your healthcare provider about the benefits and risks of treating depression during pregnancy
- are breast-feeding or plan to breast-feed. Some Lexapro may pass into your breast milk. Talk to your healthcare provider about the best way to feed your baby while taking Lexapro.

Tell your healthcare provider about all the medicines that you take, including prescription and non-prescription medicines, vitamins, and herbal supplements. Lexapro and some medicines may interact with each other, may not work as well, or may cause serious side effects.

Your healthcare provider or pharmacist can tell you if it is safe to take Lexapro with your other medicines. Do not start or stop any medicine while taking Lexapro without talking to your healthcare provider first.

If you take Lexapro, you should not take any other medicines that contain escitalopram oxalate or citalopram hydrobromide including: Celexa.

How should I take Lexapro?

- Take Lexapro exactly as prescribed. Your healthcare provider may need to change the dose of Lexapro until it is the right dose for you.
- Lexapro may be taken with or without food.
- If you miss a dose of Lexapro, take the missed dose as soon as you remember. If it is almost time for the next dose, skip the missed dose and take your next dose at the regular time. Do not take two doses of Lexapro at the same time.
- If you take too much Lexapro, call your healthcare provider or poison control center right away, or get emergency treatment.

What should I avoid while taking Lexapro?

Lexapro can cause sleepiness or may affect your ability to make decisions, think clearly, or react quickly. You should not drive, operate heavy machinery, or do other dangerous activities until you know how Lexapro affects you. Do not drink alcohol while using Lexapro.

What are the possible side effects of Lexapro?

Lexapro may cause serious side effects, including all of those described in the section entitled “What is the most important information I should know about Lexapro?”

Common possible side effects in people who take Lexapro include:

- Nausea
- Sleepiness
- Weakness
- Dizziness
- Feeling anxious
- Trouble sleeping
- Sexual problems
- Sweating
- Shaking
- Not feeling hungry
- Dry mouth
- Constipation
- Infection
- Yawning

Other side effects in children and adolescents include:

- increased thirst
- abnormal increase in muscle movement or agitation
- nose bleed
- difficult urination
- heavy menstrual periods
- possible slowed growth rate and weight change. Your child's height and weight should be monitored during treatment with Lexapro.

Tell your healthcare provider if you have any side effect that bothers you or that does not go away. These are not all the possible side effects of Lexapro. For more information, ask your healthcare provider or pharmacist.

CALL YOUR DOCTOR FOR MEDICAL ADVICE ABOUT SIDE EFFECTS. YOU MAY REPORT SIDE EFFECTS TO THE FDA AT 1-800-FDA-1088.

How should I store Lexapro?

- Store Lexapro at 25°C (77°F); excursions permitted to 15 - 30°C (59-86°F).
- Keep Lexapro bottle closed tightly.

Keep Lexapro and all medicines out of the reach of children.

General information about Lexapro

Medicines are sometimes prescribed for purposes other than those listed in a Medication Guide. Do not use Lexapro for a condition for which it was not prescribed. Do not give Lexapro to other people, even if they have the same condition. It may harm them.

This Medication Guide summarizes the most important information about Lexapro. If you would like more information, talk with your healthcare provider. You may ask your healthcare provider or pharmacist for information about Lexapro that is written for healthcare professionals.

For more information about Lexapro call 1-800-678-1605 or go to www.Lexapro.com.

What are the ingredients in Lexapro?

Active ingredient: escitalopram oxalate

Inactive ingredients:

- Tablets: talc, croscarmellose sodium, microcrystalline cellulose/colloidal silicon dioxide, and magnesium stearate. The film coating contains hypromellose, titanium dioxide, and polyethylene glycol.
- Oral Solution: sorbitol, purified water, citric acid, sodium citrate, malic acid, glycerin, propylene glycol, methylparaben, propylparaben, and natural peppermint flavor.

Forest Pharmaceuticals, Inc.
Subsidiary of Forest Laboratories, Inc.
St. Louis, MO 63045 USA

Repackaged By :
Aidarex Pharmaceuticals LLC,
Corona, CA 92880

Licensed from H. Lundbeck A/S

Revised: December 2012

This Medication Guide has been approved by the U.S. Food and Drug Administration.

© 2012 Forest Laboratories, Inc.

Principal Display Panel – 10 mg Bottle Label

NDC 33261-0699-30

Lexapro®

escitalopram oxalate

Tablets-10 mg

Equivalent to 10 mg escitalopram

30 Tablets

Rx only

FOREST PHARMACEUTICALS, INC.

Subsidiary of Forest Laboratories, Inc.

St. Louis, Missouri 63045

Repackaged By :
Aidarex Pharmaceuticals LLC,
Corona, CA 92880

Principal Display Panel – 20 mg Bottle Label

NDC 33261-0686-30

Lexapro®

escitalopram oxalate

Tablets-20 mg

Equivalent to 20 mg escitalopram

30 Tablets

Rx only

FOREST PHARMACEUTICALS, INC.

Subsidiary of Forest Laboratories, Inc.

St. Louis, Missouri 63045

Repackaged By :
Aidarex Pharmaceuticals LLC,
Corona, CA 92880